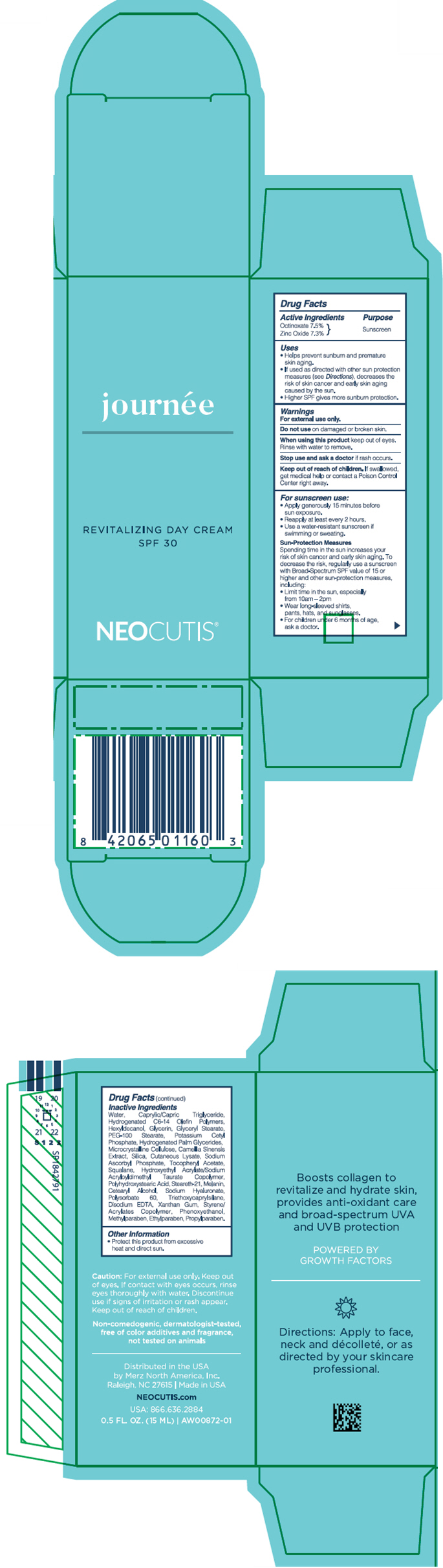 DRUG LABEL: Journee Bio-restorative Day Balm Broad-spectrum Suncreen SPF 30
NDC: 46783-002 | Form: LOTION
Manufacturer: Merz North America, Inc.
Category: otc | Type: HUMAN OTC DRUG LABEL
Date: 20251007

ACTIVE INGREDIENTS: OCTINOXATE 75 mg/1 mL; ZINC OXIDE 73 mg/1 mL
INACTIVE INGREDIENTS: WATER; EDETATE DISODIUM; METHYLPARABEN; MICROCRYSTALLINE CELLULOSE; CARBOXYMETHYLCELLULOSE SODIUM, UNSPECIFIED; GLYCERIN; XANTHAN GUM; ETHYLPARABEN; PROPYLPARABEN; POTASSIUM CETYL PHOSPHATE; CETOSTEARYL ALCOHOL; GLYCERYL MONOSTEARATE; PEG-100 MONOSTEARATE; MEDIUM-CHAIN TRIGLYCERIDES; POLYHYDROXYSTEARIC ACID (2300 MW); TRIETHOXYCAPRYLYLSILANE; HEXYLDECANOL; STEARETH-21; .ALPHA.-TOCOPHEROL ACETATE; HYALURONATE SODIUM; GREEN TEA LEAF; SODIUM ASCORBYL PHOSPHATE; PHENOXYETHANOL; MELANIN SYNTHETIC (TYROSINE, PEROXIDE); BUTYL METHACRYLATE/METHYL METHACRYLATE/METHACRYLIC ACID/STYRENE CROSSPOLYMER; SQUALANE; POLYSORBATE 60; HUMAN SKIN PROTEINS, PARTIALLY HYDROLYZED; HYDROGENATED PALM GLYCERIDES

Journée Bio-restorative Day Balm Broad-spectrum Suncreen SPF 30

Drug Facts:

Active Ingredients

Octinoxate 7.5%

Zinc Oxide 7.3%

Purpose

Sunscreen

Uses

- Helps prevent sunburn and premature skin aging.
- If used as directed with other sun protection measures (see Directions), decreases the risk of skin cancer and early skin aging caused by the sun.
- Higher SPF gives more sunburn protection.

Warnings

For external use only.

Do not use

- on damaged or broken skin.

When using this product

- keep out of eyes. Rinse with water to remove.

Stop use and ask a doctor

- if rash occurs.

Keep out of reach of children.

- If swallowed, get medical help or contact a Poison Control Center right away.

Directions

- Apply generously 15 minutes before sun exposure.
- Reapply at least every 2 hours.
- Use a water-resistant sunscreen if swimming or sweating.
- For children under 6 months of age, ask a doctor.

Sun-Protection Measures

Spending time in the sun increases your risk of skin cancer and early skin aging. To decrease the risk, regularly use a sunscreen with Broad-Spectrum SPF value of 15 or higher and other sun-protection measures including:

- Limit time in the sun, especially from 10am-2pm.
- Wear long-sleeved shirts, pants, hats, and sunglasses.

Inactive Ingredients

Water, Caprylic / Capric Triglyceride, Hydrogenated Poly (C6-14 Olefin), Hexyldecanol, Glycerin, Glyceryl Stearate, PEG-100 Stearate, Potassium Cetyl Phosphate, Hydrogenated Palm Glycerides, Microcrystalline Cellulose, Camellia Sinensis Leaf Extract, Silica, Cutaneous Lysate, Sodium Ascorbyl Phosphate, Tocopheryl Acetate, Squalane, Hydroxyethyl Acrylate / Sodium Acryloyldimethyl Taurate Copolymer, Polyhydroxystearic Acid, Steareth-21, Melanin, Cetearyl Alcohol, Sodium Hyaluronate, Polysorbate 60, Triethoxycaprylysilane, Disodium EDTA, Xanthan Gum, Styrene / Acrylates Copolymer, Phenoxyethanol, Methylparaben, Ethylparaben, Propylparaben

Other Information

- Protect this product from excessive heat and direct sun.

Distributed in the USA by Merz North America, Inc.
Raleigh, NC 27615

PRINCIPAL DISPLAY PANEL - 15 ML Bottle Carton

journée

REVITALIZING DAY CREAM
SPF 30

NEOCUTIS®